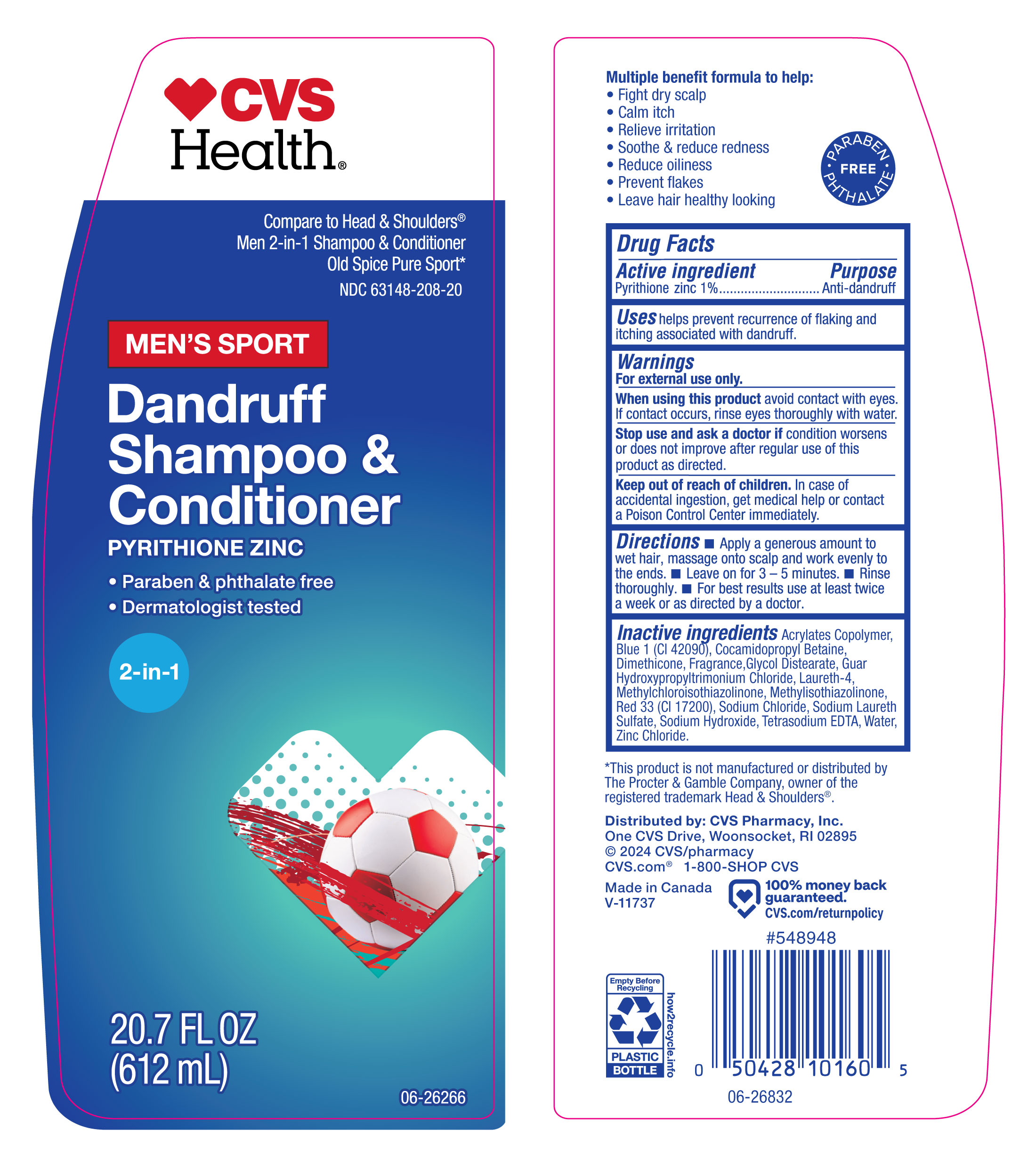 DRUG LABEL: Mens Sport
NDC: 63148-208 | Form: SHAMPOO
Manufacturer: Apollo Health and Beauty Care
Category: otc | Type: HUMAN OTC DRUG LABEL
Date: 20251010

ACTIVE INGREDIENTS: PYRITHIONE ZINC 1000 mg/100 mL
INACTIVE INGREDIENTS: ZINC CHLORIDE; RED 33; SODIUM CHLORIDE; ACRYLATES/VINYL ISODECANOATE CROSSPOLYMER (10000 MPA.S NEUTRALIZED AT 0.5%); DIMETHICONE; SODIUM HYDROXIDE; COCAMIDOPROPYL BETAINE; TETRASODIUM EDTA; DIRECT BLUE 1; GUAR HYDROXYPROPYLTRIMONIUM CHLORIDE; METHYLCHLOROISOTHIAZOLINONE; GLYCOL DISTEARATE; LAURETH-4; METHYLISOTHIAZOLINONE; WATER; FRAGRANCE CLEAN ORC0600327; SODIUM LAURETH SULFATE

63148-208, CVS Dandruff Shampoo and Conditioner- Men's Sport

Active Ingredients

Pyrithione Zinc 1%

Purpose

Anti-dandruff

Uses

Helps prevent recurrence of flaking and itching associated with dandruff.

Warnings

For External Use only

When using the product

avoid contact with eyes. If contact occurs, rinse eyes thoroughly with water.

Stop use and ask a doctor if

condition worsens or does not improve after regular use of this product as directed.

Keep out of reach of children

In case of accidental ingestion, get medical help or contact a Poison Control Center immediately.

Directions

- Apply a generous amount to wet hair, massage onto scalp and work evenly to the ends.
- Leave on for 3-5 minutes.
- Rinse throughly.
- For best results use at least twice a week or as directed by a doctor.

Inactive Ingredients

Acrylates Copolymer, Blue 1 (CI 42090), Cocamidopropyl Betaine, Dimethicone, Fragrance, Glycol Distearate, Guar Hydroxypropyltrimonium Chloride, Laureth-4, Methylchloroisothiazolinone, Methylisothiazolinone, Red 33 (CI 17200), Sodium Chloride, Sodium Laureth Sulfate, Sodium Hydroxide, Tetrasodium EDTA, Water, Zinc Chloride.